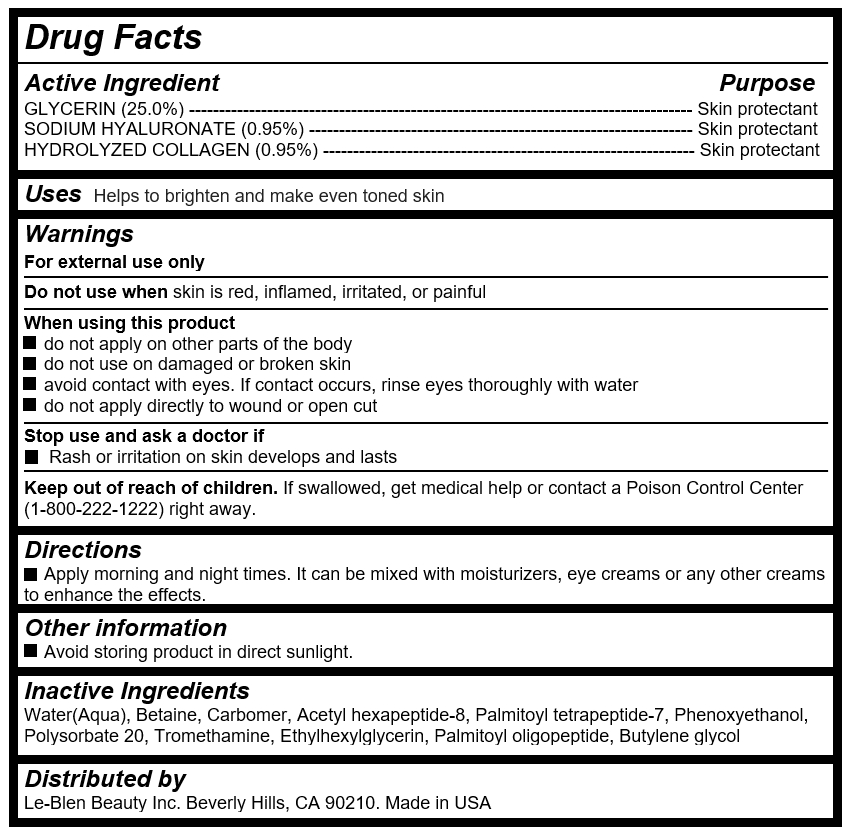 DRUG LABEL: Le-Blen Nano Collagen Peptide Serum
NDC: 72271-102 | Form: LOTION
Manufacturer: LeBlen Beauty Inc
Category: otc | Type: HUMAN OTC DRUG LABEL
Date: 20180430

ACTIVE INGREDIENTS: GLYCERIN 14.18 g/56.7 g; HYALURONATE SODIUM 0.54 g/56.7 g; PORK COLLAGEN 0.54 g/56.7 g
INACTIVE INGREDIENTS: WATER

Le-Blen Nano Collagen Peptide Serum

Active Ingredients

GLYCERIN (25.0%) ------------------------------------------------------------------------------------ Skin protectant

SODIUM HYALURONATE (0.95%) ---------------------------------------------------------------- Skin protectant

HYDROLYZED COLLAGEN (0.95%) -------------------------------------------------------------- Skin protectant

Purposes

Skin Protectant

Uses

Helps to brighten and make even toned skin

Keep out of reach of children

If swallowed, get medical help or contact a Poison Control Center (1-800-222-1222) right away.

Directions

Apply 2 or 3 drops after cleansing. Massage gently until it is absorbed.

Warnings

For external use only

Do not use when skin is red, inflamed, irritated, or painful

When using this product

do not apply on other parts of the body

do not use on damaged or broken skin

avoid contact with eyes. If contact occurs, rinse eyes thoroughly with water

do not apply directly to wound or open cut

Stop use and ask a doctor if

Rash or irritation on skin develops and lasts

Inactive Ingredients

Water(Aqua), Betaine, Carbomer, Acetyl hexapeptide-8, Palmitoyl tetrapeptide-7, Phenoxyethanol, Polysorbate 20, Tromethamine, Ethylhexylglycerin, Palmitoyl oligopeptide, Butylene glycol